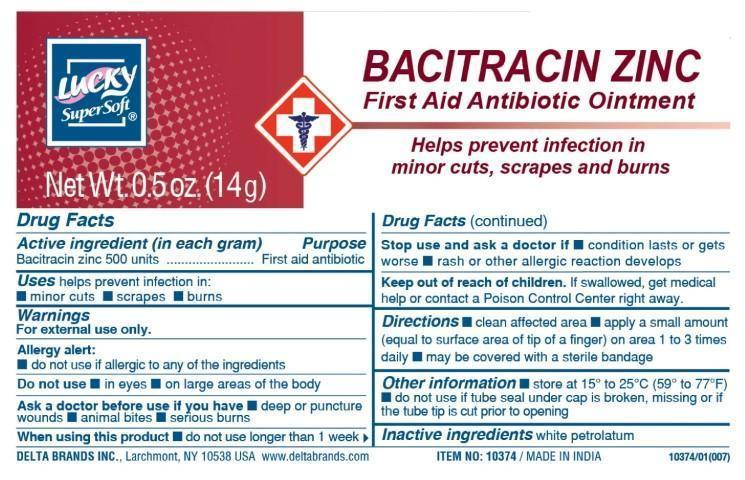 DRUG LABEL: Lucky SuperSoft

NDC: 47046-174 | Form: OINTMENT
Manufacturer: Anicare Pharmaceuticals pvt. Ltd.
Category: otc | Type: HUMAN OTC DRUG LABEL
Date: 20221122

ACTIVE INGREDIENTS: BACITRACIN ZINC 500 [USP'U]/1 g
INACTIVE INGREDIENTS: PETROLATUM

first aid - Bacitracin Zinc

Active Ingredient (in each gram)

Bacitracin zinc 500 units

Purpose

First aid antibiotic

Uses

helps prevent infection in: ■ minor cuts ■ scrapes ■ burns

Warnings

For external use only

Alergy alert

■ do not use if allergic to any of the ingredients

Do not use

■ in eyes ■ on large areas of the body

Ask a doctor before use if you have

■ deep or puncture wounds ■ animal bites ■ serious burns

When using this product ■ do not use longer than 1 week

When using this product

■ do not use longer than 1 week

Stop use and ask a doctor if

■ condition lasts or gets worse ■ rash or other allergic reaction develops

Keep out of reach of children

If swallowed, get medical help or contact a Poison Control Center right away.

Directions

■ clean the affected area ■ apply a small amount of this product (an amount equal to the surface area of the tip of a finger) on the area 1 to 3 times daily ■ may be covered with a sterile bandage

Other Information

■ store at room temperature 15-25C (59-77F)

■ do not use if tube seal under cap is broken, missing or if the tube tip is cut prior to opening

Inactive ingredients

white petrolatum